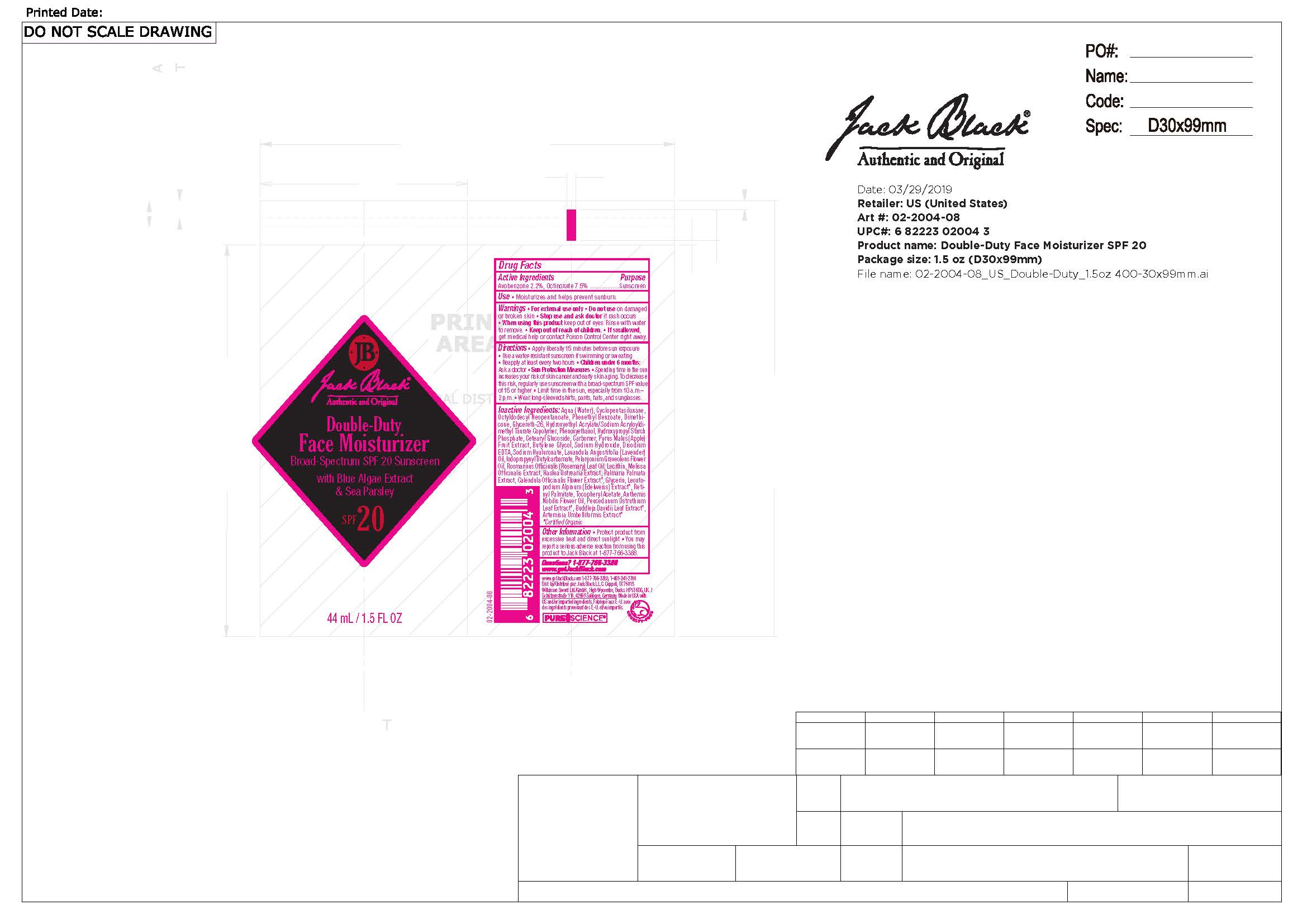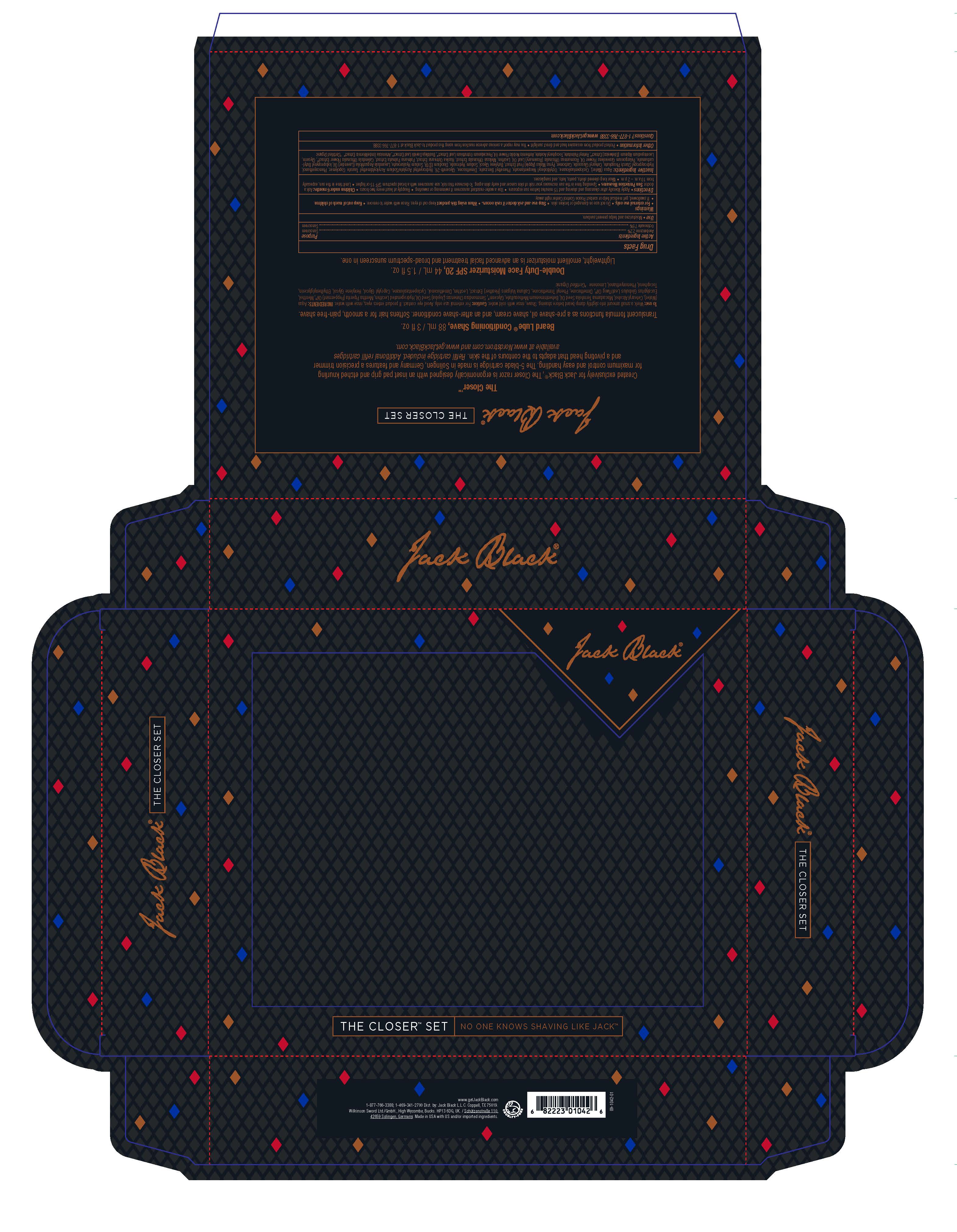 DRUG LABEL: Jack Black The Closer
NDC: 66738-421 | Form: LOTION
Manufacturer: Jack Black L.L.C
Category: otc | Type: HUMAN OTC DRUG LABEL
Date: 20210706

ACTIVE INGREDIENTS: OCTINOXATE 7.5 g/100 mL; AVOBENZONE 2.2 g/100 mL
INACTIVE INGREDIENTS: PHOSPHATIDYLCHOLINE, SOYBEAN; MELISSA OFFICINALIS; ALCOHOL; LAVENDER OIL; WATER; HYDROXYETHYL ACRYLATE/SODIUM ACRYLOYLDIMETHYL TAURATE COPOLYMER (45000 MPA.S AT 1%); HYDROXYPROPYL DISTARCH PHOSPHATE, HIGH AMYLOSE CORN; GLYCERIN; BUDDLEJA DAVIDII LEAF; PEUCEDANUM OSTRUTHIUM LEAF; BUTYLENE GLYCOL; LEUCONOSTOC/RADISH ROOT FERMENT FILTRATE; SODIUM HYDROXIDE; OCTYLDODECYL NEOPENTANOATE; PHENETHYL BENZOATE; .ALPHA.-TOCOPHEROL ACETATE; CORN OIL; HASLEA OSTREARIA; CHAMAEMELUM NOBILE FLOWER OIL; DIMETHICONE; GLYCERETH-26; APPLE; PHENOXYETHANOL; SORBITAN ISOSTEARATE; ARTEMISIA UMBELLIFORMIS FLOWER; ROSEMARY OIL; CARBOMER HOMOPOLYMER, UNSPECIFIED TYPE; HYALURONATE SODIUM; EDETATE DISODIUM ANHYDROUS; CETEARYL GLUCOSIDE; LEONTOPODIUM ALPINUM FLOWERING TOP; PELARGONIUM GRAVEOLENS FLOWER OIL; VITAMIN A PALMITATE; CALENDULA OFFICINALIS FLOWER; POLYSORBATE 60; PALMARIA PALMATA; CYCLOMETHICONE 5; IODOPROPYNYL BUTYLCARBAMATE

Active Ingredient

Avobenzone 2.2%, Octinoxate 7.5%

Purpose

Sunscreen

Use

Moisturizes and helps prevent sunburn.

Warnings

For external use only

Do not use on damaged or broken skin

Stop use and ask doctor if rash occurs

When using this product keep out of eyes. Rinse with water to remove.

Keep out of reach of children.

If swallowed, get medical help or contact Poison Control Center right away.

Directions

Apply liberally 15 minutes before sun exposure

Use a water-resistant sunscreen if swimming or sweating

Reapply at least every two hours

Children under 6 months: Ask a doctor

Sun Protection Measures • Spending time in the sun increases your risk of skin cancer and early skin aging. To decrease this risk, regularly use sunscreen with a broad-spectrum SPF value of 15 or higher • Limit time in the sun, especially from 10 a.m.–2 p.m. • Wear long-sleeved shirts, pants, hats, and sunglasses.

Inactive Ingredients

Aqua (Water), Cyclopentasiloxane, Octyldodecyl Neopentanoate, Phenethyl Benzoate, Dimethicone, Glycereth-26, Hydroxyethyl Acrylate/Sodium Acryloyldimethyl Taurate Copolymer, Phenoxyethanol, Hydroxypropyl Starch Phosphate, Cetearyl Glucoside, Carbomer, Pyrus Malus (Apple) Fruit Extract, Butylene Glycol, Sodium Hydroxide, Disodium EDTA, Sodium Hyaluronate, Lavandula Angustifolia (Lavender) Oil, Iodopropynyl Butylcarbamate, Pelargonium Graveolens Flower Oil, Rosmarinus Officinalis (Rosemary) Leaf Oil, Lecithin, Melissa Officinalis Extract, Haslea Ostrearia Extract, Palmaria Palmata Extract, Calendula Officinalis Flower Extract*, Glycerin, Leontopodium Alpinum (Edelweiss) Extract*, Retinyl Palmitate, Tocopheryl Acetate, Anthemis

Nobilis Flower Oil, Peucedanum Ostruthium Leaf Extract*, Buddleja Davidii Leaf Extract*, Artemisia Umbelliformis Extract*

*Certified Organic

Other Information

Protect product from excessive heat and direct sunlight

You may report a serious adverse reaction from using this product to Jack Black at 1-877-766-3388.

Questions?

1-877-766-3388

www.getjackblack.com